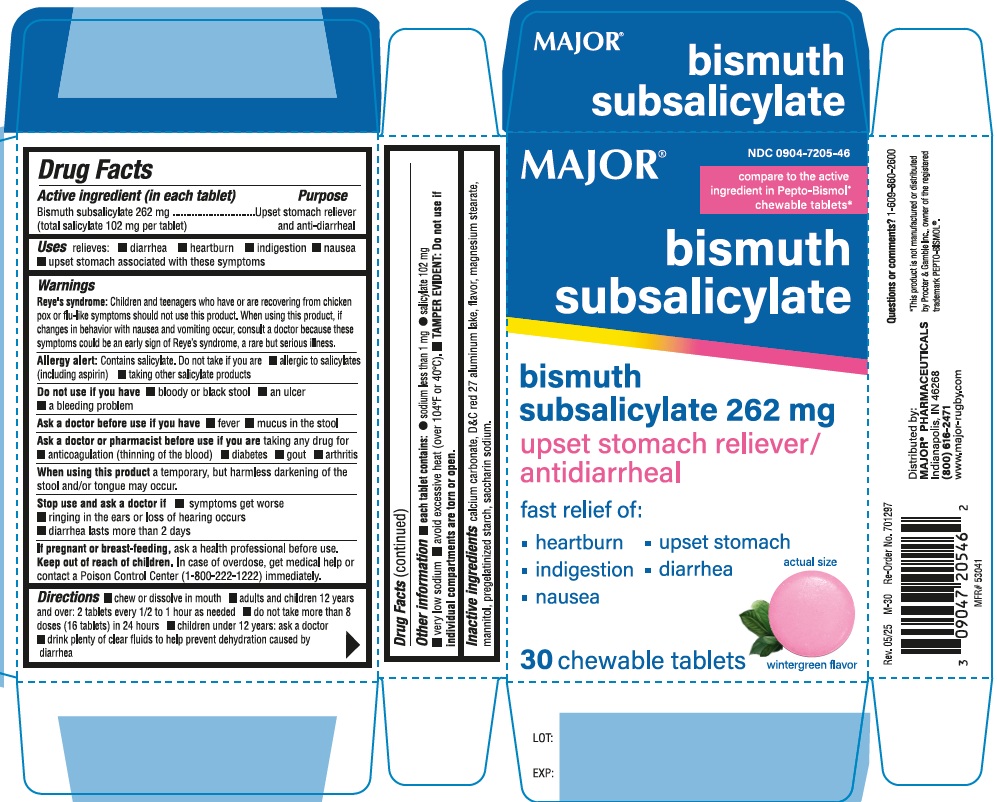 DRUG LABEL: Major Bismuth Subsalicylate
NDC: 0904-7205 | Form: TABLET, CHEWABLE
Manufacturer: Major Pharmaceuticals
Category: otc | Type: Human OTC Drug Label
Date: 20250711

ACTIVE INGREDIENTS: BISMUTH SUBSALICYLATE 262 mg/1 1
INACTIVE INGREDIENTS: CALCIUM CARBONATE; D&C RED NO. 27; MAGNESIUM STEARATE; MANNITOL; STARCH, CORN; SACCHARIN SODIUM

Major Bismuth Subsalicylate

ACTIVE INGREDIENT(in each tablet)

Bismuth subsalicylate 262 mg

(total salicylate 102 mg per tablet)

PURPOSE

Upset stomach reliever and anti-diarrheal

USE(S)

relieves:

- diarrhea
- heartburn
- indigestion
- nausea
- upset stomach associated with these symptoms

WARNINGS

Reye's Syndrome: Children and teenagers who have or are recovering from chicken pox or flu-like symptoms should not use this product. When using this product, if changes in behaviour with nausea and vomiting occur, consult a doctor because these symptoms could be an early sign of Reye's Syndrome, a rare but serious illness.

Allergy alert: Contains salicylate. Do not take if you are

- allergic to salicylates (including aspirin)
- taking other salicylate products

DO NOT USE IF YOU HAVE

- bloody or black stool
- an ulcer
- a bleeding problem

ASK A DOCTOR BEFORE USE IF YOU HAVE

- fever
- mucus in the stool

ASK A DOCTOR OR PHARMACIST BEFORE USE IF YOU ARE

taking any drug for

- anticoagulation (thinning of the blood)
- diabetes
- gout
- arthritis

WHEN USING THIS PRODUCT

a temporary, but harmless darkening of the stool and/or tongue may occur

STOP USE AND ASK DOCTOR IF

- symptoms get worse
- ringing in the ears or loss of hearing occurs
- diarrhea lasts more than 2 days

IF PREGNANT OR BREAST-FEEDING,

ask a health professional before use.

KEEP OUT OF REACH OF CHILDREN

In case of overdose, get medical help or contact a Poison Control Center (1-800-222-1222) immediately.

DIRECTIONS

- chew or dissolve in mouth
- adults and children 12 years and over: 2 tablets every 1/2 to 1 hour as needed
- do not take more than 8 doses (16 tablets) in 24 hours
- children under 12 years: ask a doctor
- drink plenty of clear fluids to help prevent dehydration caused diarrhea

OTHER INFORMATION

- each tablet contains:
- sodium less than 1 mg
- salicylate 102 mg
- very low sodium
- avoid excessive heat (over 104oF or 40oC)
- TAMPER EVIDENT: Do not use if individual compartments are torn on open.

INACTIVE INGREDIENTS

calcium carbonate, D&C red 27 aluminum lake, flavor, magnesium stearate, mannitol, pregelatinized starch, saccharin sodium

PRINCIPAL DISPLAY PANEL

MAJOR

NDC 0904-7205-46
*Compare to the active ingredient in Pepto-Bismol®

Bismuth Subsalicylate 262 mg

Upset Stomach Reliever / Anti-diarrheal
Soothing, coating action provides fast relief for

heartburn, indigestion

nausea, upset stomach

and diarrhea

30 Chewable Tablets